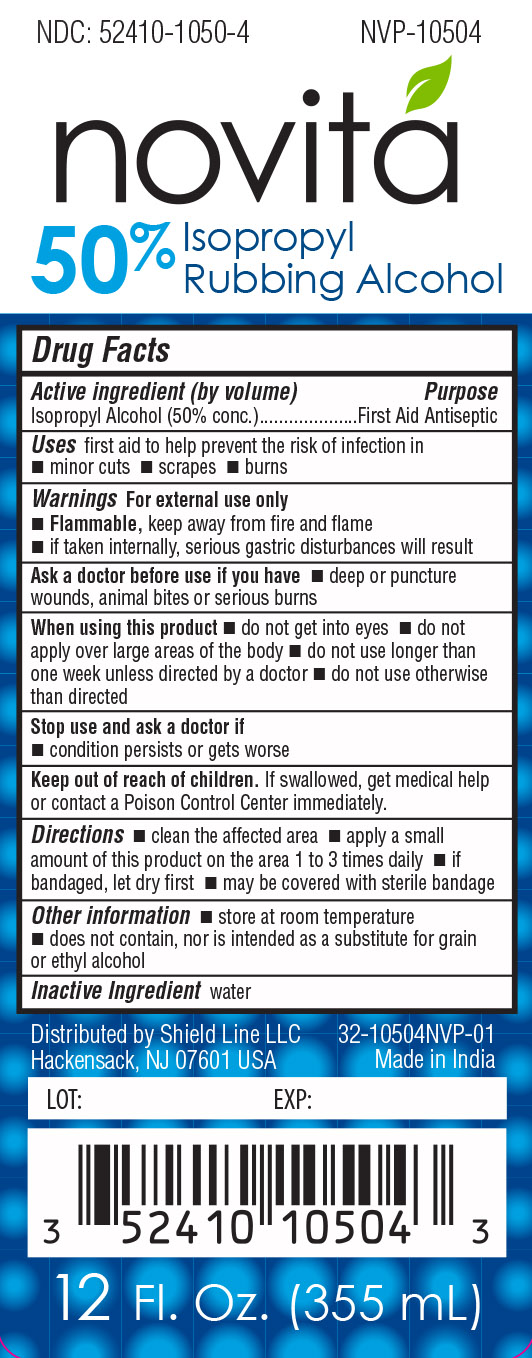 DRUG LABEL: NOVITA ISOPROPYL ALCOHOL 50%
NDC: 52410-1050 | Form: LIQUID
Manufacturer: Shield Line LLC
Category: otc | Type: HUMAN OTC DRUG LABEL
Date: 20240417

ACTIVE INGREDIENTS: ISOPROPYL ALCOHOL 50 mL/100 mL
INACTIVE INGREDIENTS: WATER

Active Ingredients

Isopropyl Alcohol (50% v/v)

Purpose

First Aid Antiseptic

Uses

first aid to help prevent the risk of infection in

- minor cuts
- scrapes
- burns

Warnings For external use only

- Flammable, keep away from fire and flame
- if taken internally, serious gastric disturbances will result

Ask a doctor before use if you have

- deep or puncture wounds
- animal bites
- serious burns

When using this product

- do not get into eyes
- do not apply over large areas of the body
- do not use longer than one week unless directed by a doctor
- do not use otherwise than directed

Stop use and ask a doctor if

- condition persists or gets worse

Keep out of reach of children

If swallowed, get medical help or contact a Poison Control Center immediately

Directions

- clean the affected area
- apply a small amount of this product on the area 1 to 3 times daily
- if bandaged, lets dry first
- may be covered with sterile bandage

Other information

- store at room temperature
- does not contain, nor is intended as a substitute for grain or ethyl alcohol

Inactive Ingredient

water